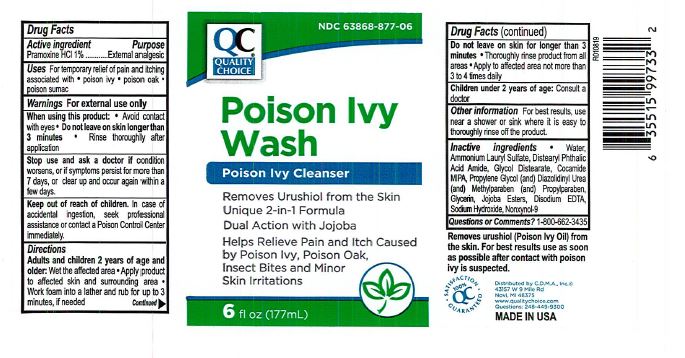 DRUG LABEL: Poison Ivy Wash
NDC: 63868-877 | Form: LOTION
Manufacturer: Chain Drug Market Association
Category: otc | Type: HUMAN OTC DRUG LABEL
Date: 20231220

ACTIVE INGREDIENTS: PRAMOXINE HYDROCHLORIDE 10 mg/1 mL
INACTIVE INGREDIENTS: GLYCOL DISTEARATE; PROPYLENE GLYCOL; DIAZOLIDINYL UREA; METHYLPARABEN; WATER; AMMONIUM LAURYL SULFATE; HYDROLYZED JOJOBA ESTERS (ACID FORM); EDETATE DISODIUM; NONOXYNOL-9; PROPYLPARABEN; GLYCERIN; SODIUM HYDROXIDE

QC Poison Ivy Wash

ACTIVE INGREDIENT

Pramoxine HCl 1%

PURPOSE

External Analgesic

INDICATIONS AND USAGE

For temporary relief of pain and itching associated with poison ivy, poison oak, and poison sumac.

WARNINGS

For external use only.

When using this product:

Avoid Contact with eyes.

Do not leave on skin longer than 3 minutes

Rinse thoroughly after application

When using this product avoid contact with the eyes. Do not leave on skin longer than 3 minutes. Rinse thoroughly after application.

Stop use and ask a doctor if condition worses, or if symptoms persist for more than 7 days or clear up and occur again within a few days.

DOSAGE AND ADMINISTRATION

Adults and children 2 years of age and older: wet the affected area, apply product to affected skin and surrounding area. work foam into lather and rub for up to 3 minutes if needed. do not leave on skin for longer than 3 minutes. Thoroughly rinse product form all areas. Apply to affected are not more than 3 to 4 times daily.

INACTIVE INGREDIENT

Water

ammonium lauryl sulfare

distearyl phtalic acid amide

glycol distereate

cocamide MIPA

Propylene glycol

Diazolidyn Urea

Methylparaben
Propylparaben

Glycerin

Jojoba esters

disodium edta

sodium hydroxide

nonoxynol-9

Keep out of reach of children. In case of accidental ingestion, seek professional assistance or contact a poison control center immediately.